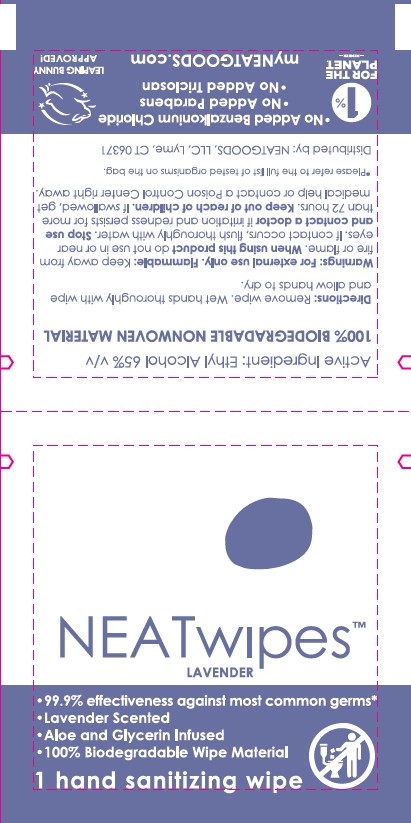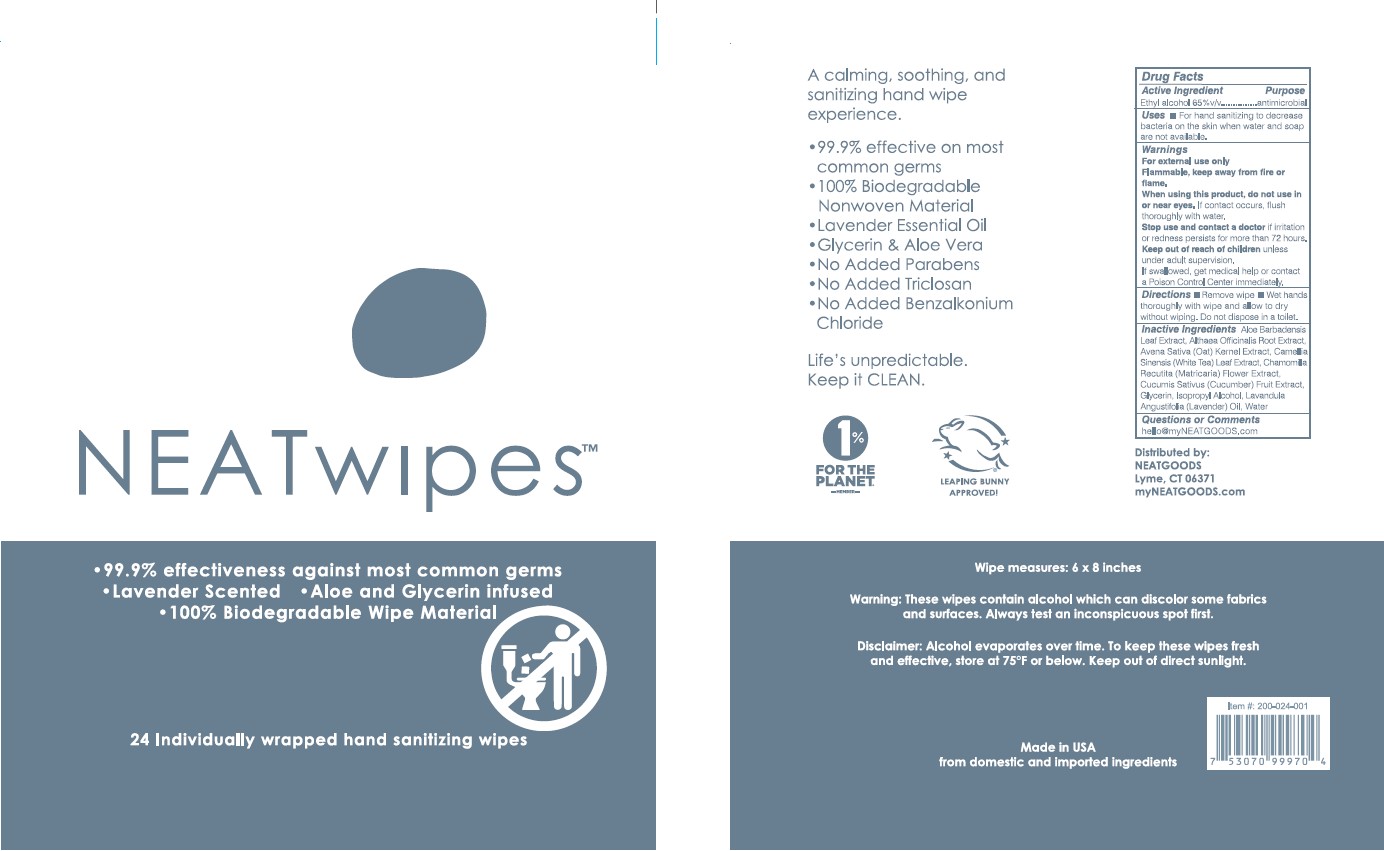 DRUG LABEL: Hand Sanitizing Wipe
NDC: 81339-100 | Form: CLOTH
Manufacturer: NeatGoods LLC
Category: otc | Type: HUMAN OTC DRUG LABEL
Date: 20251201

ACTIVE INGREDIENTS: ALCOHOL 65 mL/100 mL
INACTIVE INGREDIENTS: ALOE VERA LEAF; OAT; CUCUMBER; LAVENDER OIL; WATER; ALTHAEA OFFICINALIS ROOT; GREEN TEA LEAF; CHAMOMILE; GLYCERIN

NEATwipes

Active Ingredient

Ethyl Alcohol – 65% v/v

Purpose

antimicrobial

Uses

■ For hand sanitizing to decrease bacteria on the skin when water and soap are not available.

Warnings

For external use only

Flammable, keep away from fire or flame.

When using this product, do not use in or near eyes. If contact occurs, flush thoroughly with water.

Stop use and contact a doctor if irritation or redness persists for more than 72 hours.

Keep out of reach of children unless under adult supervision.

If swallowed, get medical help or contact a Poison Control Center immediately.

Directions

■ Remove wipe

■ Wet hands thoroughly with wipe and allow to dry without wiping. Do not dispose in a toilet.

Inactive Ingredients

Aloe Barbadensis Leaf Extract, Althaea Officinalis Root Extract, Avena Sativa (Oat) Kernel Extract, Camellia Sinensis (White Tea) Leaf Extract, Chamomilla Recutita (Matricaria) Flower Extract, Cucumis Sativus (Cucumber) Fruit Extract, Glycerin, Isopropyl Alcohol, Lavandula Angustifolia (Lavender) Oil, Water

Questions or Comments

hello@myNEATGOODS.com

Label

NEATwipes™

• 99.9% effectiveness against most common germs • Lavender Scented • Aloe and Glycerin infused • 100% Biodegradable wipe Material

24 Individually wrapped hand sanitizing wipes

A calming, soothing, and sanitizing hand wipe experience.

• 99.9% effective on most common germs

• 100% Biodegradable Nonwoven Material

• Lavender Essential Oil

• Glycerin & Aloe Vera

• No Added Parabens

• No Added Triclosan

• No Added Benzalkonium Chloride

Life's unpredictable. Keep it CLEAN.

1% FOR THE PLANET. -MEMBER-

LEAPING BUNNY APPROVED!

Drug Facts

Active Ingredient Purpose

Ethyl Alcohol 65%..............antimicrobial

Uses ■ For hand sanitizing to decrease bacteria on the skin when water and soap are not available.

Warnings

For external use only

Flammable, Keep away from fire or flame.

When using this product, do not use in or near eyes. If contact occurs, flush thoroughlt with water,

Stop use and contact a doctor if irritation or redness persists for more than 72 hours.

Keep out of reach of children unless under adult supervision. If swallowed, get medical help or contact a Poison Control Center immediately.

Discontinue ■ Remove wipe ■ Wet hands thoroughly with wipe and allow to dry without wiping. Do not dispose in a toilet.

Inactive ingredients Aloe Barbadensis Leaf Extract, Althaea Officinalis Root Extract, Avena Sativa (Oat) Kernel Extract, Camellia Sinensis (White Tea) Leaf Extract, Chamomilla Recutita (Matricaria) Flower Extract, Cucumis Sativus (Cucumber) Fruit Extract, Glycerin, Isopropyl Alcohol, Lavandula Angustifolia (Lavender) Oil, Water

Questions or Comments hello@myNEATGOODS.com

Distributed by: NEATGOODS Lyme, CT 06371

myNEATGOODS.COM

100% BIODEGRADABLE WIPE MATERIAL

Directions: Remove wipe. Wet hands thoroughly with wipe and allow to dry.

For external use only

Warnings: For external use only. Flammable: Keep away from fire or flame.

When using this product do not use in or near eyes.

If contact occurs, flush thoroughly with water.

Stop use and contact a doctor if irritation and redness persists for more than 72 hours.

Keep out of reach of children. If swallowed, get medical help or contact a Poison Control Center right away.

Distributed by:

NEATGOODS Lyme, CT 06371

my NEATGOODS.COM

Wipe measures: 6 x 8 inches

Warning: These wipes contain alcohol which can discolor same fabrics

and surfaces. Always test an inconspicuous spot first.

Disclaimer: Alcohol evaporates over time. To keep these wipes fresh

and effective, store at 75ºF or below. Keep out of direct sunlight.

Made in USA

from domestic and imported ingredients

Item #: 200-024-001

7 53070 99970 4

NEATwipes™

LAVENDER

• 99.9% effectiveness against most common germs* • Lavender Scented • Aloe and Glycerin infused • 100% Biodegradable wipe Material

1 hand sanitizing wipe

Active Ingredient: Ethyl Alcohol 65% v/v

100% BIODEGRADABLE NONWOVEN MATERIAL

Directions: Remove wipe. Wet hands thoroughly with wipe and allow hands to dry.

For external use only

Warnings: For external use only. Flammable: Keep away from fire or flame. When using this product do not use in or near eyes. If contact occurs, flush thoroughly with water. Stop use and contact a doctor if irritation and redness persists for more than 72 hours. Keep out of reach of children. If swallowed, get medical help or contact a Poison Control Center right away.

*Please refer to the full list of tested organisms on the bag.

Distributed by: NEATGOODS, LLC, Lyme, CT 06371

1% FOR THE PLANET. -MEMBER-

• No Added Benzalkonium Chloride

• No Added Parabens

• No Added Triclosan

myNEATGOODS.COM

LEAPING BUNNY APPROVED!